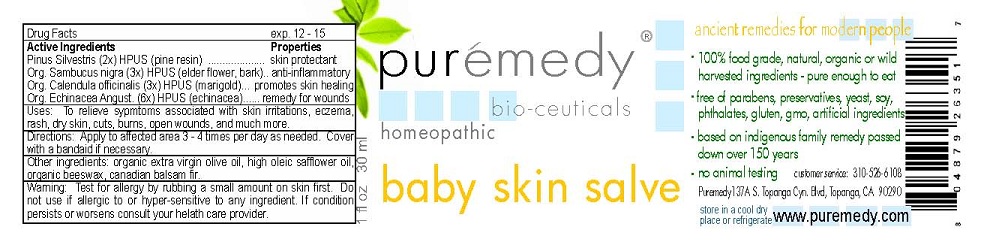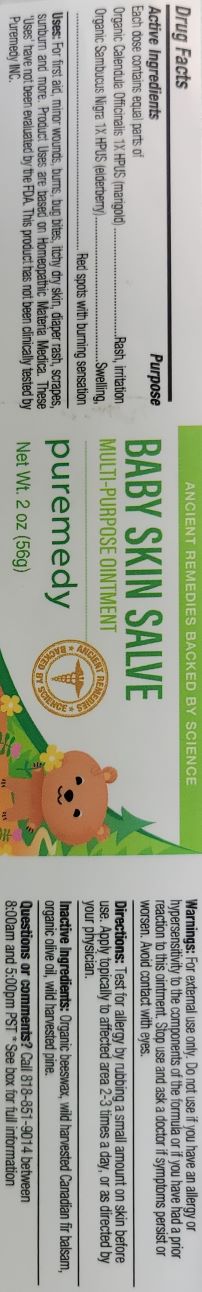 DRUG LABEL: BABY SKIN
NDC: 52810-201 | Form: SALVE
Manufacturer: PUREMEDY
Category: homeopathic | Type: HUMAN OTC DRUG LABEL
Date: 20211006

ACTIVE INGREDIENTS: ECHINACEA ANGUSTIFOLIA 6 [hp_X]/100 mL; SAMBUCUS NIGRA FLOWER 3 [hp_X]/100 mL; CALENDULA OFFICINALIS FLOWER 3 [hp_X]/100 mL; PINE NEEDLE OIL (PINUS SYLVESTRIS) 2 [hp_X]/100 mL
INACTIVE INGREDIENTS: OLIVE OIL; SAFFLOWER OIL; YELLOW WAX; ABIES BALSAMEA LEAF OIL

BABY SKIN SALVE (52810-201)

ACTIVE INGREDIENTS

PINUS SILVESTRIS (2X) HPUS (PINE RESIN)

ORG. SAMBUCUS NIGRA (3X) HPUS (ELDERBERRY)

ORG. CALENDULA OFFICINALIS (6X) HPUS (MARIGOLD)

ORG. ECHINACEA ANGUSTIFOLIA (6X) HPUS (ECHINACEA)

PURPOSE

PROPERTIES

SKIN PROTECTANT

ANTI-INFLAMMATORY

PROMOTES SKIN HEALING

REMEDY FOR WOUNDS

INDICATIONS AND USAGE

USES: TO RELIEVE SYMPTOMS ASSOCIATED WITH SKIN IRRITATIONS, ECZEMA, RASH, DRY SKIN, CUTS, BURNS, OPEN WOUNDS, AND MUCH MORE.

DOSAGE AND ADMINISTRATION

DIRECTIONS: APPLY TO AFFECTED AREA 3-4 TIMES PER DAY AS NEEDED. COVER WITH A BANDAID IF NECESSARY.

INACTIVE INGREDIENT

OTHER INGREDIENTS: ORGANIC EXTRA VIRGIN OLIVE OIL, HIGH OLEIC SAFFLOWER OIL, ORGANIC BEESWAX, CANADIAN BALSAM FIR.

WARNINGS

WARNING: TEST FOR ALLERGY BY RUBBING A SMALL AMOUNT ON SKIN FIRST. DO NOT USE IF ALLERGIC TO OR HYPER-SENSITIVE TO ANY INGREDIENT IN THIS SALVE. IF CONDITION PERSISTS OR WORSENS CONSULT YOUR HEALTH CARE PROVIDER.

KEEP OUT OF REACH OF CHILDREN.

OTHER SAFETY INFORMATION

STORE IN A COOL DRY PLACE OR REFRIGERATE